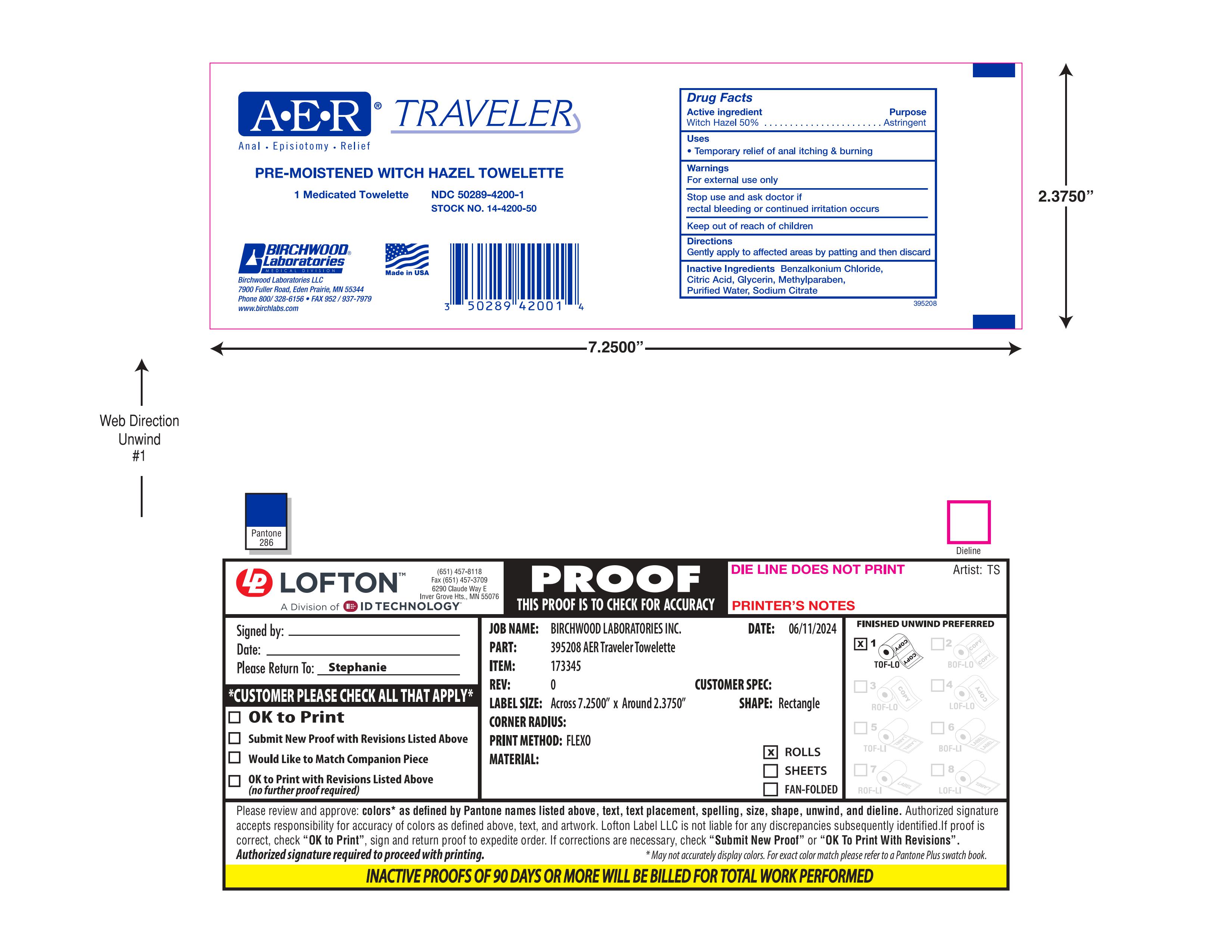 DRUG LABEL: AER Traveler Towelette
NDC: 50289-4200 | Form: SOLUTION
Manufacturer: Birchwood Laboratories LLC
Category: otc | Type: HUMAN OTC DRUG LABEL
Date: 20260108

ACTIVE INGREDIENTS: WITCH HAZEL 0.5 g/1 1
INACTIVE INGREDIENTS: BENZALKONIUM CHLORIDE; GLYCERIN; SODIUM CITRATE; WATER; ANHYDROUS CITRIC ACID; METHYLPARABEN

ACTIVE INGREDIENT

Witch Hazel 50%

PURPOSE

Astringent

INDICATIONS AND USAGE

Temporary relief of anal itching & burning

WARNINGS

For external use only

Stop use and ask doctor if rectal bleeding or continued irritation occurs

Stop use and ask doctor if rectal bleeding or continued irritation occurs

Keep out of reach of children

INSTRUCTIONS FOR USE

Gently apply to affected areas by patting and then discard

INACTIVE INGREDIENT

Benzalkonium Chloride, Citric Acid, Glycerin, Methylparaben, Purified Water, Sodium Citrate

DESCRIPTION

PRE-MOISTENED WITCH HAZEL TOWELETTE

DOSAGE AND ADMINISTRATION

Gently apply to affected areas by patting and then discard